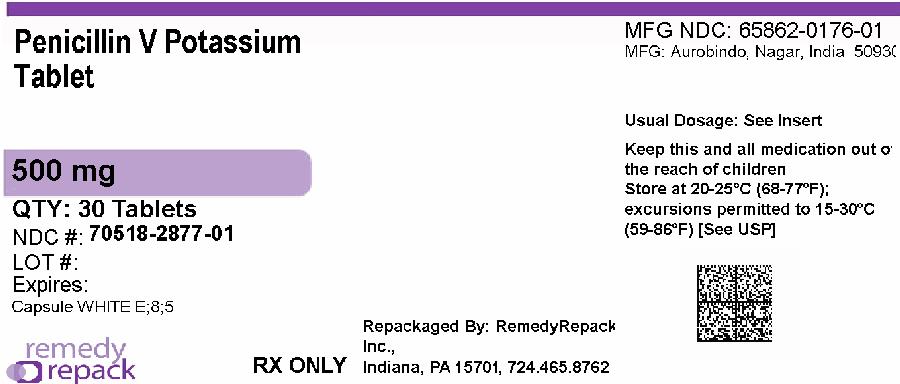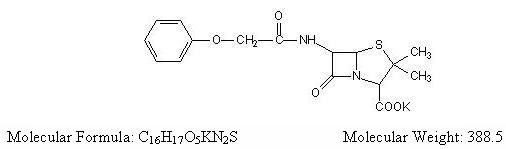 DRUG LABEL: Penicillin V Potassium
NDC: 70518-2877 | Form: TABLET, FILM COATED
Manufacturer: REMEDYREPACK INC.
Category: prescription | Type: HUMAN PRESCRIPTION DRUG LABEL
Date: 20260213

ACTIVE INGREDIENTS: PENICILLIN V POTASSIUM 500 mg/1 1
INACTIVE INGREDIENTS: POVIDONE K90; MICROCRYSTALLINE CELLULOSE; TALC; SILICON DIOXIDE; MAGNESIUM STEARATE; HYPROMELLOSE 2910 (6 MPA.S); POLYETHYLENE GLYCOL 400; TITANIUM DIOXIDE

Penicillin V Potassium Tablets, USP
Rx only

To reduce the development of drug-resistant bacteria and maintain the effectiveness of penicillin V potassium and other antibacterial drugs, penicillin V potassium should be used only to treat or prevent infections that are proven or strongly suspected to be caused by bacteria.

DESCRIPTION

Penicillin V is the phenoxymethyl analog of penicillin G. Penicillin V potassium is the potassium salt of penicillin V.

Penicillin V potassium tablets, for oral administration, contain 250 mg (400,000 units) or 500 mg (800,000 units). The 250 mg tablet is equivalent to 250 mg (400,000 units) penicillin V and the 500 mg tablet is equivalent to 500 mg (800,000 units) penicillin V. In addition, each tablet contains the following inactive ingredients: povidone, microcrystalline cellulose, talc, colloidal silicon dioxide, magnesium stearate, hypromellose, polyethylene glycol, and titanium dioxide.

CLINICAL PHARMACOLOGY

Penicillin V exerts a bactericidal action against penicillin-sensitive microorganisms during the stage of active multiplication. It acts through the inhibition of biosynthesis of cell-wall mucopeptide. It is not active against the penicillinase-producing bacteria, which include many strains of staphylococci. The drug exerts high in vitroactivity against staphylococci (except penicillinase-producing strains), streptococci (groups A, C, G, H, L and M), and pneumococci. Other organisms sensitive in vitroto penicillin V are Corynebacterium diphtheriae, Bacillus anthracis, Clostridia, Actinomyces bovis, Streptobacillus moniliformis, Listeria monocytogenes, Leptospira,and Neisseria gonorrhoeae. Treponema pallidumis extremely sensitive.
The potassium salt of penicillin V has the distinct advantage over penicillin G in resistance to inactivation by gastric acid. It may be given with meals; however, blood levels are slightly higher when the drug is given on an empty stomach. Average blood levels are two to five times higher than the levels following the same dose of oral penicillin G and also show much less individual variation.
Once absorbed, penicillin V is about 80% bound to serum protein. Tissue levels are highest in the kidneys, with lesser amounts in the liver, skin, and intestines. Small amounts are found in all other body tissues and the cerebrospinal fluid. The drug is excreted as rapidly as it is absorbed in individuals with normal kidney function; however, recovery of the drug from the urine indicates that only about 25% of the dose given is absorbed. In neonates, young infants, and individuals with impaired kidney function, excretion is considerably delayed.

Microbiology

Susceptibility Testing

For specific information regarding susceptibility test interpretive criteria and associated test methods and quality control standards recognized by FDA for this drug, please see: https://www.fda.gov/STIC.

INDICATIONS AND USAGE

To reduce the development of drug-resistant bacteria and maintain the effectiveness of penicillin V potassium and other antibacterial drugs, penicillin V potassium should be used only to treat or prevent infections that are proven or strongly suspected to be caused by susceptible bacteria. When culture and susceptibility information are available, they should be considered in selecting or modifying antibacterial therapy. In the absence of such data, local epidemiology and susceptibility patterns may contribute to the empiric selection of therapy.
Penicillin V potassium tablets are indicated in the treatment of mild to moderately severe infections due to penicillin G-sensitive microorganisms. Therapy should be guided by bacteriologic studies (including sensitivity tests) and by clinical response.
NOTE: Severe pneumonia, empyema, bacteremia, pericarditis, meningitis, and arthritis should not be treated with penicillin V during the acute stage. Indicated surgical procedures should be performed.
The following infections will usually respond to adequate dosage of penicillin V.
Streptococcal Infections (without bacteremia)
Mild-to-moderate infections of the upper respiratory tract, scarlet fever, and mild erysipelas.
NOTE: Streptococci in groups A, C, G, H, L, and M are very sensitive to penicillin. Other groups, including group D (enterococcus), are resistant.
Pneumococcal Infections
Mild to moderately severe infections of the respiratory tract.
Staphylococcal infections– penicillin G-sensitive
Mild infections of the skin and soft tissues.
NOTE: Reports indicate an increasing number of strains of staphylococci resistant to penicillin G, emphasizing the need for culture and sensitivity studies in treating suspected staphylococcal infections.
Fusospirochetosis (Vincent’s gingivitis and pharyngitis)
Mild to moderately severe infections of the oropharynx usually respond to therapy with oral penicillin.
NOTE: Necessary dental care should be accomplished in infections involving the gum tissue.
Medical conditions in which oral penicillin therapy is indicated as prophylaxis: For the prevention of recurrence following rheumatic fever and/or chorea: Prophylaxis with oral penicillin on a continuing basis has proven effective in preventing recurrence of these conditions.
Although no controlled clinical efficacy studies have been conducted, penicillin V has been suggested by the American Heart Association and the American Dental Association for use as an oral regimen for prophylaxis against bacterial endocarditis in patients who have congenital heart disease or rheumatic or other acquired valvular heart disease when they undergo dental procedures and surgical procedures of the upper respiratory tract^1. Oral penicillin should not be used in those patients at particularly high risk for endocarditis (e.g., those with prosthetic heart valves or surgically constructed systemic pulmonary shunts). Penicillin V should not be used as adjunctive prophylaxis for genitourinary instrumentation or surgery, lower-intestinal tract surgery, sigmoidoscopy, and childbirth. Since it may happen that alphahemolytic streptococci relatively resistant to penicillin may be found when patients are receiving continuous oral penicillin for secondary prevention of rheumatic fever, prophylactic agents other than penicillin may be chosen for these patients and prescribed in addition to their continuous rheumatic fever prophylactic regimen.
NOTE: When selecting antibiotics for the prevention of bacterial endocarditis, the physician or dentist should read the full joint statement of the American Heart Association and the American Dental Association^1.

CONTRAINDICATIONS

A previous hypersensitivity reaction to any penicillin is a contraindication.

WARNINGS

SERIOUS AND OCCASIONALLY FATAL HYPERSENSITIVITY (anaphylactic) REACTIONS HAVE BEEN REPORTED IN PATIENTS ON PENICILLIN THERAPY. THESE REACTIONS ARE MORE LIKELY TO OCCUR IN INDIVIDUALS WITH A HISTORY OF PENICILLIN HYPERSENSITIVITY AND/OR A HISTORY OF SENSITIVITY TO MULTIPLE ALLERGENS. THERE HAVE BEEN REPORTS OF INDIVIDUALS WITH A HISTORY OF PENICILLIN HYPERSENSITIVITY WHO HAVE EXPERIENCED SEVERE REACTIONS WHEN TREATED WITH CEPHALOSPORINS. BEFORE INITIATING THERAPY WITH PENICILLIN V POTASSIUM TABLETS, CAREFUL INQUIRY SHOULD BE MADE CONCERNING PREVIOUS HYPERSENSITIVITY REACTIONS TO PENICILLINS, CEPHALOSPORINS, OR OTHER ALLERGENS. IF AN ALLERGIC REACTION OCCURS, PENICILLIN V POTASSIUM TABLETS SHOULD BE DISCONTINUED AND APPROPRIATE THERAPY INSTITUTED. SERIOUS ANAPHYLACTIC REACTIONS REQUIRE IMMEDIATE EMERGENCY TREATMENT WITH EPINEPHRINE. OXYGEN, INTRAVENOUS STEROIDS, AND AIRWAY MANAGEMENT, INCLUDING INTUBATION, SHOULD ALSO BE ADMINISTERED AS INDICATED.
Clostridium difficile associated diarrhea (CDAD) has been reported with use of nearly all antibacterial agents, including penicillin V potassium tablets, and may range in severity from mild diarrhea to fatal colitis. Treatment with antibacterial agents alters the normal flora of the colon leading to overgrowth of C. difficile.
C. difficile produces toxins A and B which contribute to the development of CDAD. Hypertoxin producing strains of C. difficilecause increased morbidity and mortality, as these infections can be refractory to antimicrobial therapy and may require colectomy. CDAD must be considered in all patients who present with diarrhea following antibiotic use. Careful medical history is necessary since CDAD has been reported to occur over two months after the administration of antibacterial agents.
If CDAD is suspected or confirmed, ongoing antibiotic use not directed against C. difficilemay need to be discontinued. Appropriate fluid and electrolyte management, protein supplementation, antibiotic treatment of C. difficile, and surgical evaluation should be instituted as clinically indicated.

PRECAUTIONS

Penicillin should be used with caution in individuals with histories of significant allergies and/or asthma.

General

Prescribing penicillin V potassium in the absence of a proven or strongly suspected bacterial infection or a prophylactic indication is unlikely to provide benefit to the patient and increases the risk of the development of drug-resistant bacteria.
The oral route of administration should not be relied upon in patients with severe illness, or with nausea, vomiting, gastric dilatation, cardiospasm, or intestinal hypermotility.
Occasionally patients will not absorb therapeutic amounts of orally administered penicillin.
In streptococcal infections, therapy must be sufficient to eliminate the organism (10-day minimum); otherwise the sequelae of streptococcal disease may occur. Cultures should be taken following completion of treatment to determine whether streptococci have been eradicated.
Prolonged use of antibiotics may promote the overgrowth of nonsusceptible organisms, including fungi. Should superinfection occur, appropriate measures should be taken.

Information for Patients

Patients should be counseled that antibacterial drugs including penicillin V potassium should only be used to treat bacterial infections. They do not treat viral infections (e.g., the common cold). When penicillin V potassium is prescribed to treat a bacterial infection, patients should be told that although it is common to feel better early in the course of therapy, the medication should be taken exactly as directed. Skipping doses or not completing the full course of therapy may: (1) decrease the effectiveness of the immediate treatment, and (2) increase the likelihood that bacteria will develop resistance and will not be treatable by penicillin V potassium or other antibacterial drugs in the future.
Diarrhea is a common problem caused by antibiotics which usually ends when the antibiotic is discontinued. Sometimes after starting treatment with antibiotics, patients can develop watery and bloody stools (with or without stomach cramps and fever) even as late as two or more months after having taken the last dose of the antibiotic. If this occurs, patients should contact their physician as soon as possible.

Repackaged By / Distributed By: RemedyRepack Inc.

625 Kolter Drive, Indiana, PA 15701

(724) 465-8762

ADVERSE REACTIONS

Although the incidence of reactions to oral penicillins has been reported with much less frequency than following parenteral therapy, it should be remembered that all degrees of hypersensitivity, including fatal anaphylaxis, have been reported with oral penicillin.
The most common reactions to oral penicillin are nausea, vomiting, epigastric distress, diarrhea, and black hairy tongue. The hypersensitivity reactions reported are skin eruptions (maculopapular to exfoliative dermatitis), urticaria and other serum-sickness like reactions, laryngeal edema, and anaphylaxis.
Fever and eosinophilia may frequently be the only reaction observed. Hemolytic anemia, leukopenia, thrombocytopenia, neuropathy, and nephropathy are infrequent reactions and usually associated with high doses of parenteral penicillin.

DOSAGE AND ADMINISTRATION

The dosage of Penicillin V should be determined according to the sensitivity of the causative microorganisms and the severity of infection, and adjusted to the clinical response of the patient.
The usual dosage recommendations for adults and children 12 years and over are as follows:
Streptococcal Infections
Mild to moderately severe - of the upper respiratory tract and including scarlet fever and erysipelas: 125 to 250 mg (200,000 to 400,000 units) every 6 to 8 hours for 10 days.
Pneumococcal Infections
Mild to moderately severe - of the respiratory tract, including otitis media: 250 to 500 mg (400,000 to 800,000 units) every 6 hours until the patient has been afebrile for at least 2 days.
Staphylococcal Infections
Mild infections of skin and soft tissue (culture and sensitive tests should be performed): 250 to 500 mg (400,000 to 800,000 units) every 6 to 8 hours.
Fusospirochetosis (Vincent’s infection)of the oropharynx. Mild to moderately severe infections: 250 to 500 mg (400,000 to 800,000 units) every 6 to 8 hours.
For the prevention of recurrence following rheumatic fever and/or chorea: 125 mg to 250 mg (200,000 to 400,000 units) twice daily on a continuing basis.
For prophylaxis against bacterial endocarditis^1in patients with congenital heart disease or rheumatic or other acquired valvular heart disease when undergoing dental procedures or surgical procedures of the upper respiratory tract: 2 gram of penicillin V (1 gram for children under 60 lbs.) 1 hour before the procedure, and then, 1 gram (500 mg for children under 60 lbs.) 6 hours later.

HOW SUPPLIED

Penicillin V Potassium Tablets USP, 500 mg (800,000 units) are white to off-white, capsule shaped, film-coated tablets, debossed with ‘E’ and a breakline on one side and ‘8’ and ‘5’ separated with a breakline on the other side.

NDC: 70518-2877-00

NDC: 70518-2877-01

PACKAGING: 20 in 1 BOTTLE PLASTIC

PACKAGING: 30 in 1 BOTTLE PLASTIC

Store at 20° to 25°C (68° to 77°F); excursions permitted to 15° to 30°C (59° to 86°F) [see USP Controlled Room Temperature].

Dispense in a tight container, as defined in the USP.

Keep tightly closed.

Keep out of reach of children.

Repackaged and Distributed By:

Remedy Repack, Inc.

625 Kolter Dr. Suite #4 Indiana, PA 1-724-465-8762

REFERENCES

1. American Heart Association.1984. Prevention of bacterial endocarditis. Circulation 70(6):1123A – 1127A.

Repackaged and Distributed By:

Remedy Repack, Inc.

625 Kolter Dr. Suite #4 Indiana, PA 1-724-465-8762

PACKAGE LABEL

DRUG: Penicillin V Potassium

GENERIC: Penicillin V Potassium

DOSAGE: TABLET, FILM COATED

ADMINSTRATION: ORAL

NDC: 70518-2877-0

NDC: 70518-2877-1

COLOR: white

SHAPE: CAPSULE

SCORE: Two even pieces

SIZE: 17 mm

IMPRINT: E;8;5

PACKAGING: 20 in 1 BOTTLE, PLASTIC

PACKAGING: 30 in 1 BOTTLE, PLASTIC

ACTIVE INGREDIENT(S):

- PENICILLIN V POTASSIUM 500mg in 1

INACTIVE INGREDIENT(S):

- POVIDONE K90
- MICROCRYSTALLINE CELLULOSE
- TALC
- SILICON DIOXIDE
- MAGNESIUM STEARATE
- HYPROMELLOSE 2910 (6 MPA.S)
- POLYETHYLENE GLYCOL 400
- TITANIUM DIOXIDE